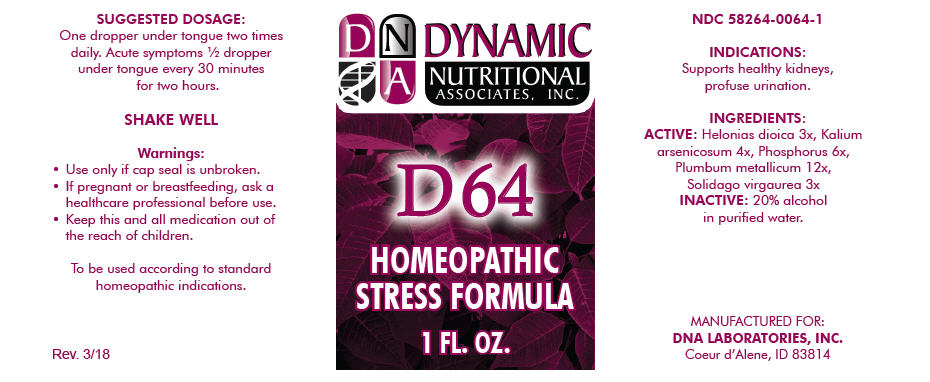 DRUG LABEL: D-64
NDC: 58264-0064 | Form: SOLUTION
Manufacturer: DNA Labs, Inc.
Category: homeopathic | Type: HUMAN OTC DRUG LABEL
Date: 20250113

ACTIVE INGREDIENTS: CHAMAELIRIUM LUTEUM ROOT 3 [hp_X]/1 mL; POTASSIUM ARSENITE ANHYDROUS 4 [hp_X]/1 mL; PHOSPHORUS 6 [hp_X]/1 mL; LEAD 12 [hp_X]/1 mL; SOLIDAGO VIRGAUREA FLOWERING TOP 3 [hp_X]/1 mL
INACTIVE INGREDIENTS: ALCOHOL; WATER

D-64

NDC 58264-0064-1

INDICATIONS

PURPOSE

Supports healthy kidneys, profuse urination.

INGREDIENTS

ACTIVE

Helonias dioica 3x, Kalium arsenicosum 4x, Phosphorus 6x, Plumbum metallicum 12x, Solidago virgaurea 3x

INACTIVE

20% alcohol in purified water.

SUGGESTED DOSAGE

One dropper under tongue two times daily. Acute symptoms ½ dropper under tongue every 30 minutes for two hours.

STORAGE AND HANDLING

SHAKE WELL

Warnings

- Use only if cap seal is unbroken.

PREGNANCY OR BREAST FEEDING

- If pregnant or breastfeeding, ask a healthcare professional before use.

KEEP OUT OF REACH OF CHILDREN

- Keep this and all medication out of the reach of children.

To be used according to standard homeopathic indications.

PRINCIPAL DISPLAY PANEL - 1 FL. OZ. Bottle Label

DYNAMIC
NUTRITIONAL
ASSOCIATES, INC.

D 64

HOMEOPATHIC
STRESS FORMULA

1 FL. OZ.